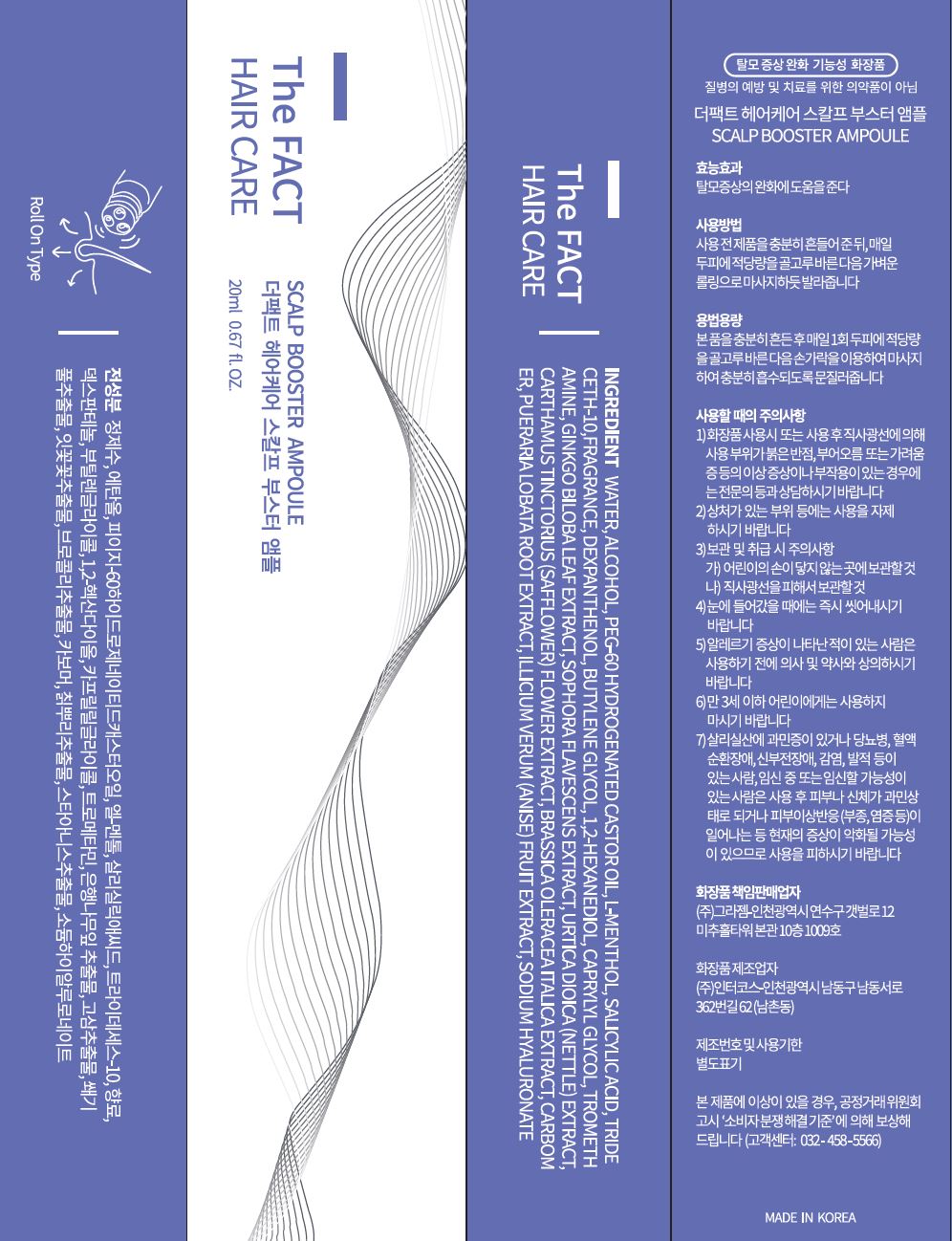 DRUG LABEL: The Fact Hair Care Scalp Booster Ampoule
NDC: 77049-0013 | Form: LIQUID
Manufacturer: Interkos Co.,Ltd.
Category: otc | Type: HUMAN OTC DRUG LABEL
Date: 20230211

ACTIVE INGREDIENTS: DEXPANTHENOL 0.2 g/100 mL; LEVOMENTHOL 0.3 g/100 mL; SALICYLIC ACID 0.25 g/100 mL
INACTIVE INGREDIENTS: BUTYLENE GLYCOL; WATER

Drug Facts

ACTIVE INGREDIENT

-menthol, Salicylic acid, Dexpanthenol

INACTIVE INGREDIENT

Water
Alcohol
PEG-60 Hydrogenated Castor Oil
Trideceth-10
Fragrance
Butylene Glycol
1,2-Hexanediol
Caprylyl Glycol
Tromethamine
Ginkgo Biloba Leaf Extract
Sophora Flavescens Extract
Urtica Dioica (Nettle) Extract
Carthamus Tinctorius (Safflower) Flower Extract
Brassica Oleracea Italica Extract
Carbomer
Pueraria Lobata Root Extract
Illicium Verum (Anise) Fruit Extract
Sodium Hyaluronate

PURPOSE

Helps treat hair loss symptoms

KEEP OUT OF REACH OF THE CHILDREN

INDICATIONS AND USAGE

Shake the product thoroughly, then apply evenly onto the scalp with the massage roller.

WARNINGS

1) After application, if there are any abnormal symptoms or side effects such as red spots, swelling, or itching in the area from direct sunlight, please consult with a specialist.

2) Avoid using the product on areas with scarring or open wounds.

3) Storage and handling

A) Keep out of reach of children

B) Keep away from direct sunlight

4) Keep out of eyes, if this occurs, rinse immediately with water

5) For any adverse allergic reactions, please consult your doctor or pharmacist before use.

6) Not for children under the age of 3

7) Those with diabetes, blood circulation disorder, renal failure, infection, redness, hypersensitivity to salicylic acid, etc., and those who are pregnant or likely to become pregnant may experience skin or body hypersensitivity or skin adverse reactions (edema, inflammation, etc.). Avoid using the product if symptoms arise

DOSAGE AND ADMINISTRATION

external use only